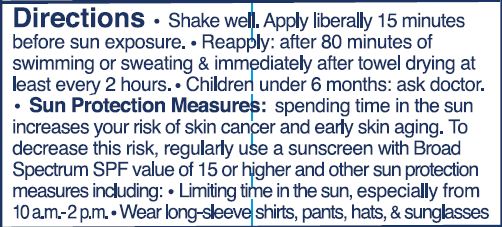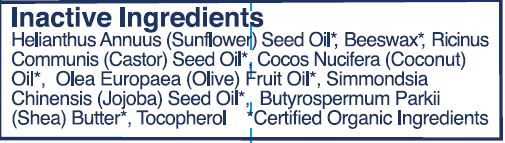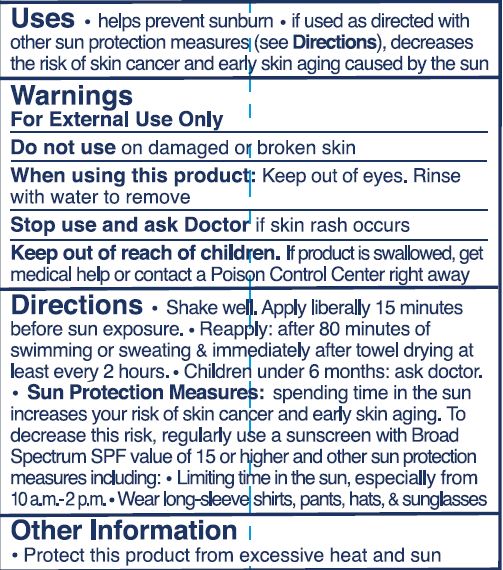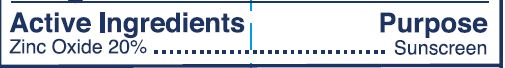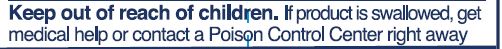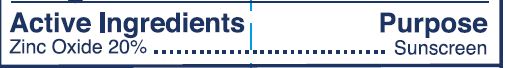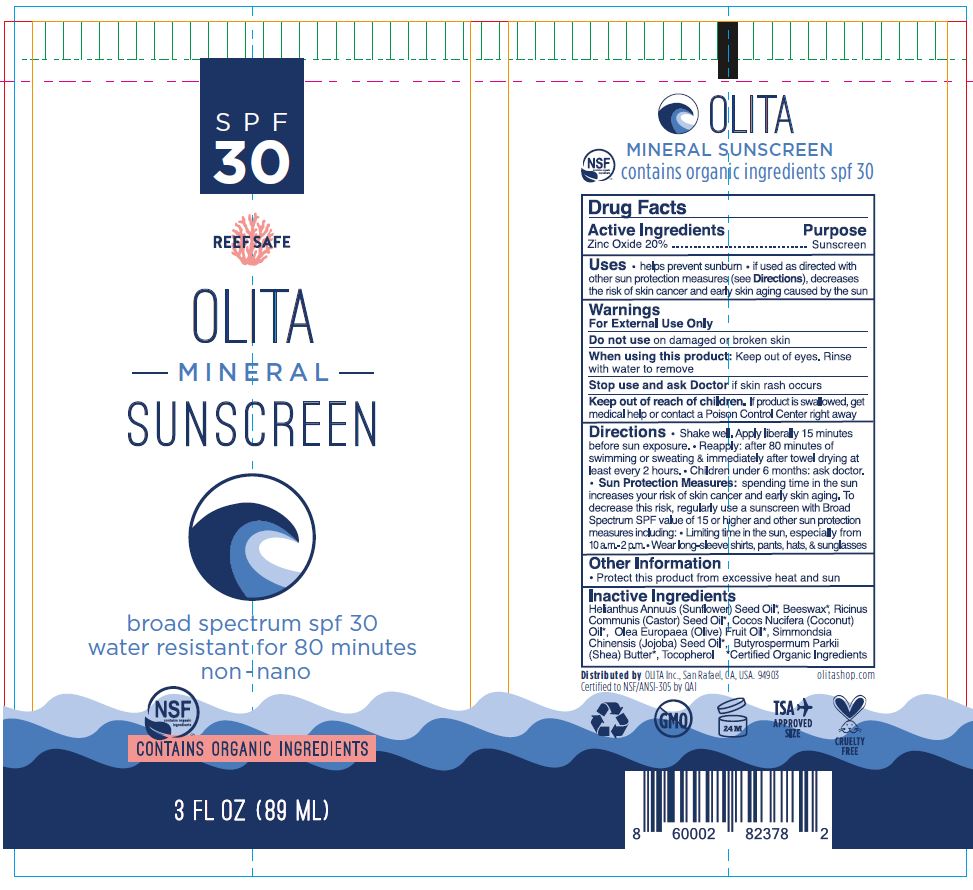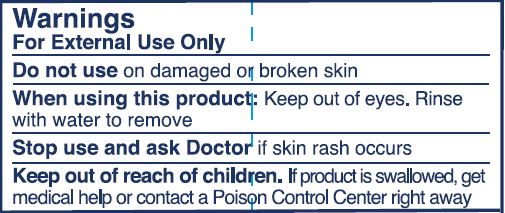 DRUG LABEL: Sunscreen
NDC: 62932-216 | Form: OINTMENT
Manufacturer: Private Label Select Ltd CO
Category: otc | Type: HUMAN OTC DRUG LABEL
Date: 20200201

ACTIVE INGREDIENTS: ZINC OXIDE 20 g/100 g
INACTIVE INGREDIENTS: JOJOBA OIL; SUNFLOWER OIL; .BETA.-TOCOPHEROL; WHITE WAX; SHEA BUTTER; CASTOR OIL; COCONUT OIL; OLIVE OIL

Olita Mineral Sunscreen, SPF 30